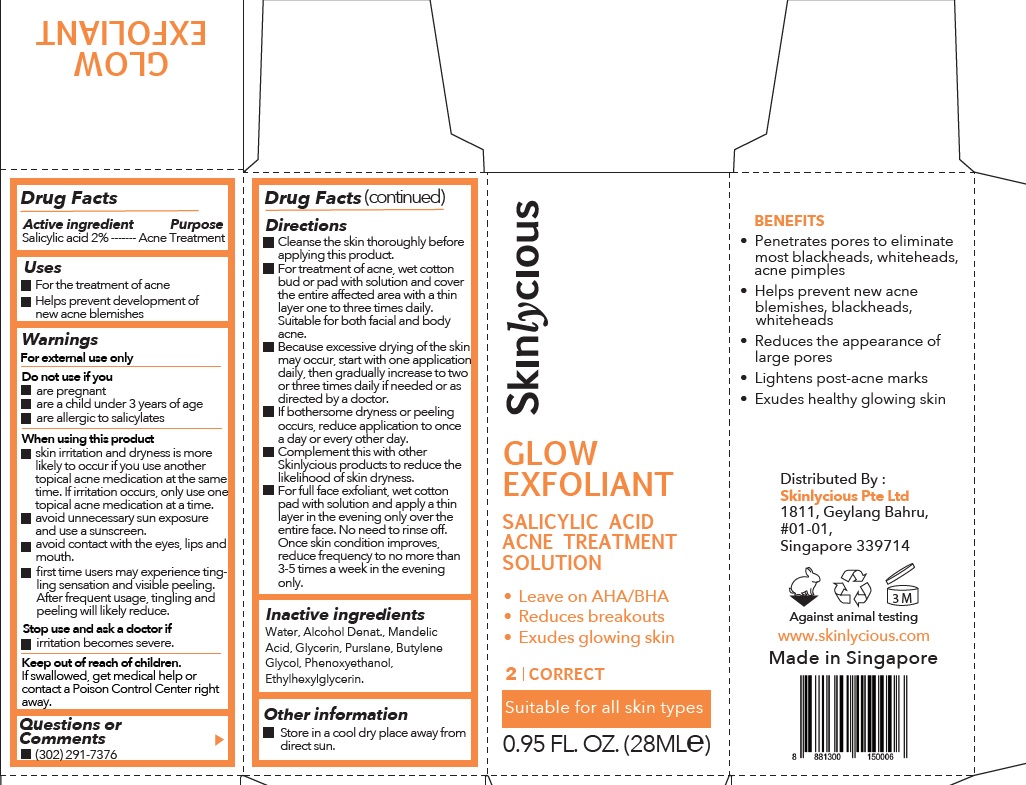 DRUG LABEL: Skinlycious Glow Exfoliant
NDC: 81574-001 | Form: LIQUID
Manufacturer: Skinlycious Pte Ltd
Category: otc | Type: HUMAN OTC DRUG LABEL
Date: 20251003

ACTIVE INGREDIENTS: SALICYLIC ACID 2 g/100 mL
INACTIVE INGREDIENTS: WATER; ALCOHOL; MANDELIC ACID; GLYCERIN; PURSLANE; BUTYLENE GLYCOL; PHENOXYETHANOL; ETHYLHEXYLGLYCERIN

Active ingredient

Salicylic Acid 2%

Purpose

Acne treatment

Uses

• For the treatment of acne
• Helps prevent development of new acne blemishes

Warnings

For External Use Only
Do not use if you
• are pregnant
• are a child under 3 years of age
• are allergic to salicylates

When using this product
• skin irritation and dryness is more likely to occur if you use another topical acne medication at the same time. If irritation occurs, only use one topical acne medication at a time.
• Avoid unnecessary sun exposure and use a sunscreen.
• Avoid contact with the eyes, lips and mouth.
• First time users may experience tingling sensation and visible peeling. After frequent usage, tingling and peeling will likely reduce.

Stop use and ask a doctor if
• Irritation becomes severe

Keep out of reach of children

If swallowed, get medical help or contact a Poison Control Center right away.

Questions or Comments

(302) 291-7376

Direction

• Cleanse the skin thoroughly before applying this product
• For treatment of acne, wet cotton bud or pad with solution and cover the entire affected area with a thin layer one to three times daily. Suitable for both facial and body acne.
• Because excessive drying of the skin may occur, start with one application daily, then gradually increase to two or three times daily if needed or as directed by a doctor.
• If bothersome dryness or peeling occurs, reduce application to once a day or every other day.
• Complement this with other Skinlycious products to reduce the likelihood of skin dryness.
• For full face exfoliant, wet cotton pad with a solution and apply a thin layer in the evening only over the entire face. No need to rinse off. Once skin condition improves, reduce frequency to no more than 3-5 times a week in the evening only.

Inactive Ingredients

Water, Alcohol Denat. Mandelic Acid, Glycerin, Purslane, Butylene Glycol, Phenoxyethanol, Ethylhexylglycerin.

Other information

• Store in a cool dry place away from direct sun.